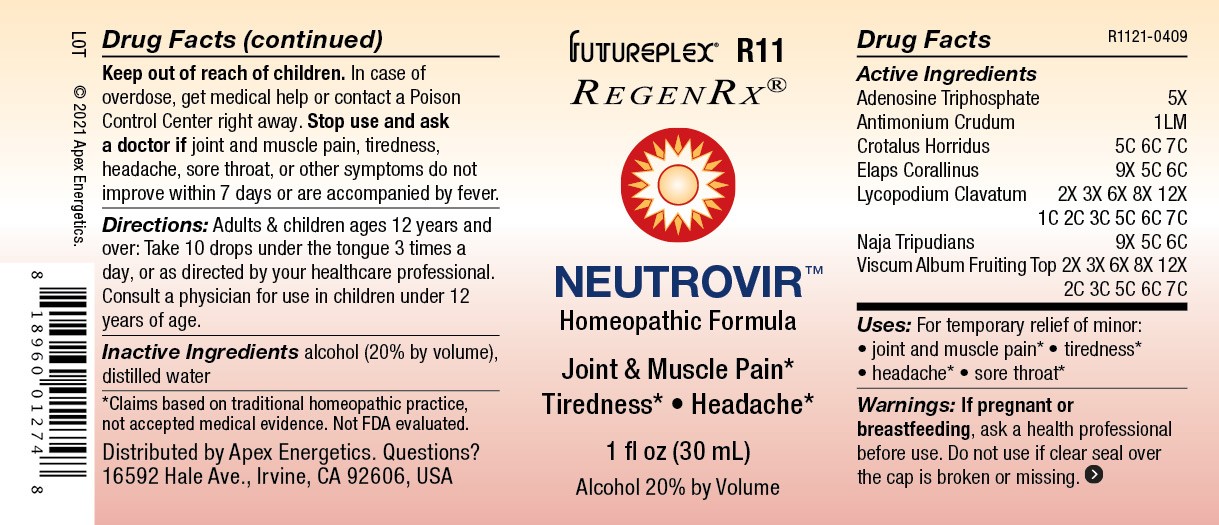 DRUG LABEL: R11
NDC: 63479-1811 | Form: SOLUTION/ DROPS
Manufacturer: Apex Energetics Inc.
Category: homeopathic | Type: HUMAN OTC DRUG LABEL
Date: 20240108

ACTIVE INGREDIENTS: MICRURUS CORALLINUS VENOM 6 [hp_C]/1 mL; LYCOPODIUM CLAVATUM SPORE 7 [hp_C]/1 mL; VISCUM ALBUM FRUITING TOP 7 [hp_C]/1 mL; ADENOSINE TRIPHOSPHATE 5 [hp_X]/1 mL; ANTIMONY TRISULFIDE 1 [hp_Q]/1 mL; CROTALUS HORRIDUS HORRIDUS VENOM 7 [hp_C]/1 mL; NAJA NAJA VENOM 6 [hp_C]/1 mL
INACTIVE INGREDIENTS: ALCOHOL; WATER

R11

Active Ingredients
Adenosine Triphosphate | 5X
Antimonium Crudum | 1LM
Crotalus Horridus | 5C 6C 7C
Elaps Corallinus | 9X 5C 6C
Lycopodium Clavatum | 2X 3X 6X 8X 12X 1C 2C 3C 5C 6C 7C
Naja Tripudians | 9X 5C 6C
Viscum Album Fruiting Top | 2X 3X 6X 8X 12X 2C 3C 5C 6C 7C

INDICATIONS AND USAGE

Uses:

For temporary relief of minor:

joint and muscle pain*

tiredness*

headache*

sore throat*

*Claims based on traditional homeopathic practice, not accepted medical evidence. Not FDA evaluated.

Warnings:

PREGNANCY OR BREAST FEEDING

If pregnant or breastfeeding, ask a health professional before use.

Do not use if clear seal over the cap is broken or missing.

Keep out of reach of children. In case of overdose, get medical help or contact a Poison Control Center right away.

Stop use and ask a doctor if joint and muscle pain, tiredness, headache, sore throat, or other symptoms do not improve within 7 days or are accompanied by fever.

Directions:

Adults & children ages 12 years and over: Take 10 drops under the tongue 3 times a day, or as directed by your healthcare professional. Consult a physician for use in children under 12 years of age.

Inactive Ingredients

alcohol (20% by volume), distilled water

Distributed by Apex Energetics. Questions?

16592 Hale Ave., Irvine, CA 92606, USA

PACKAGE LABEL

FUTUREPLEX® R11

REGENRX®

NEUTROVIR™

Homeopathic Formula

Joint & Muscle Pain*

Tiredness* • Headache*

1 fl oz (30 mL)

Alcohol 20% by Volume